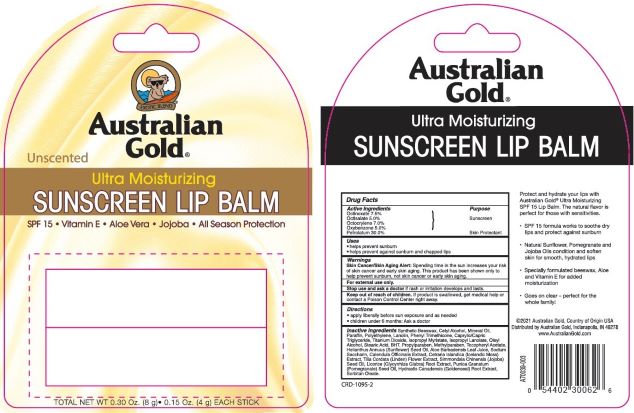 DRUG LABEL: Australian Gold SPF 15 Lip Balm
NDC: 84061-128 | Form: STICK
Manufacturer: Australian Gold
Category: otc | Type: HUMAN OTC DRUG LABEL
Date: 20260122

ACTIVE INGREDIENTS: OCTINOXATE 7.5 mg/1 g; OXYBENZONE 5 mg/1 g; PETROLATUM 30 mg/1 g; OCTOCRYLENE 7 mg/1 g; OCTISALATE 5 mg/1 g
INACTIVE INGREDIENTS: LIGHT MINERAL OIL 7 mg/1 g; .ALPHA.-TOCOPHEROL ACETATE 0.1 mg/1 g; WHITE WAX 16.8 mg/1 g; CETYL ALCOHOL 7 mg/1 g; METHYLPARABEN 0.1 mg/1 g

Drug Facts

Active ingredient

Octinoxate (7.5%), Octocrylene (7.0%), Oxybenzone (5.0%), Octisalate (5.0%), Petrolatum (30.0%)

Purpose

Sunscreen, Sunscreen, Sunscreen, Sunscreen, Skin Protectant

Keep Out of Reach of Children

If swallowed get medical help or contact a Poison Control Center right away.

Uses

Prevents Sunburns

Warnings

Skin Cancer/Skin Aging Alert: Spending time in the sun increases your risk of skin cancer and early skin aging. This product has been shown only to prevent sunburn, not skin cancer or early aging.

For external use only: Stop use and ask a doctor: if rash or irritation develops and lasts.

Directions

Apply liberally before sun exposure and as needed. Children under 6 months of age: Ask a doctor before use.

Inactive Ingredients

Synthetic Beeswax, Cetyl Alcohol, Mineral Oil, Paraffin, Polyethylene, Flavor, Caprylic/Capric Triglyceride, Titanium Dioxide (CI 77891), Stearic Acid, Aluminum Hydroxide, Lanolin, Phenyl Trimethicone, Oleyl Alcohol, Isopropyl Lanolate, Isopropyl Myristate, BHT, Tocopheryl Acetate, Propyl paraben, Aloe Barbadensis Leaf Extract, Methylparaben, Sodium Saccharin.